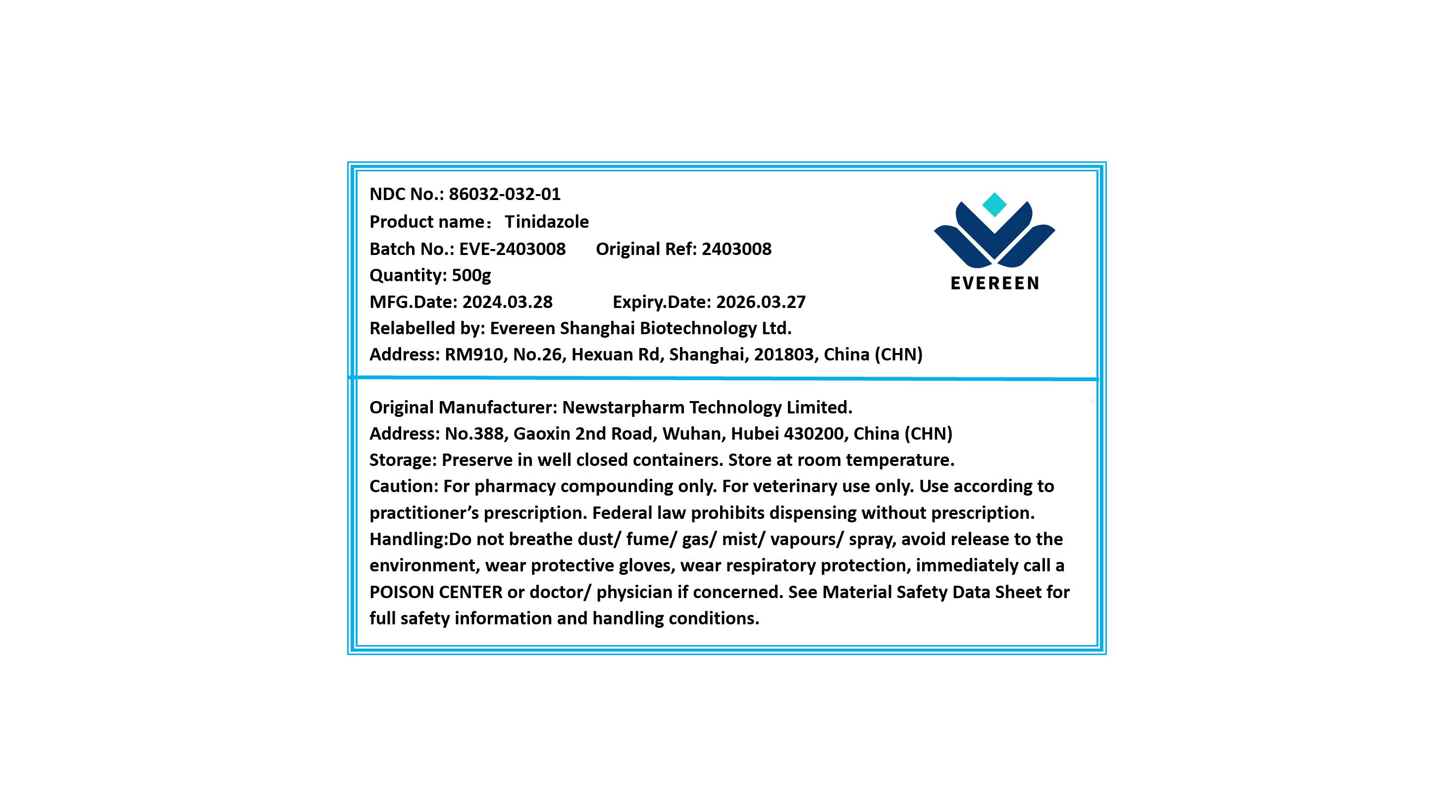 DRUG LABEL: Tinidazole
NDC: 86032-032 | Form: POWDER
Manufacturer: Evereen Shanghai Biotechnology Ltd.
Category: other | Type: BULK INGREDIENT - ANIMAL DRUG
Date: 20241030

ACTIVE INGREDIENTS: TINIDAZOLE 1 g/1 g

Tinidazole